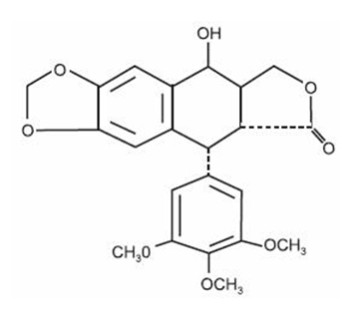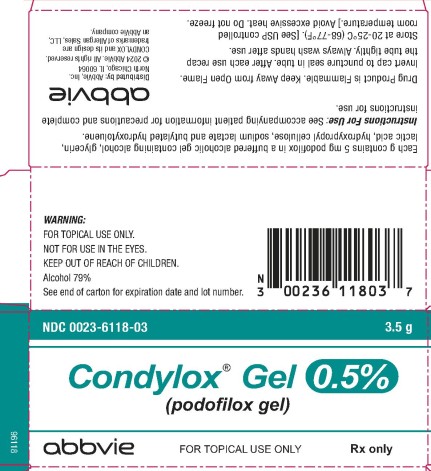 DRUG LABEL: Condylox
NDC: 0023-6118 | Form: GEL
Manufacturer: Allergan, Inc.
Category: prescription | Type: HUMAN PRESCRIPTION DRUG LABEL
Date: 20240129

ACTIVE INGREDIENTS: PODOFILOX 5 mg/1 g
INACTIVE INGREDIENTS: ALCOHOL; GLYCERIN; LACTIC ACID, UNSPECIFIED FORM; HYDROXYPROPYL CELLULOSE (1600000 WAMW); SODIUM LACTATE; BUTYLATED HYDROXYTOLUENE

Physician Information
Condylox® Gel 0.5%
(podofilox gel)
(con' de lox)
Content Updated: January 2024
Rx only

DESCRIPTION

Podofilox is an antimitotic drug which can be chemically synthesized or purified from the plant families Coniferae and Berberidaceae (e.g. species of Juniperus and Podophyllum). Condylox Gel 0.5% is formulated for topical administration. Each gram of gel contains 5 mg of podofilox in a buffered alcoholic gel containing alcohol, glycerin, lactic acid, hydroxypropyl cellulose, sodium lactate, and butylated hydroxytoluene.

Podofilox has a molecular weight of 414.4 daltons, and is soluble in alcohol and sparingly soluble in water. Its chemical name is [5R,-(5α, 5aβ, 8aα, 9α]-5,8,8a,9-tetrahydro-9-hydroxy-5-(3,4,5-trimethoxyphenyl) furo[3',4':6,7]naphtho-[2,3,-d]-1,3-dioxol-6(5aH)-one.

Podofilox has the following structural formula:

CLINICAL PHARMACOLOGY

Mechanism of Action

Treatment of anogenital warts with podofilox results in necrosis of visible wart tissue. The exact mechanism of action is unknown.

Pharmacokinetics

In systemic absorption studies in 52 patients, topical application of 0.05 mL of an ethanolic solution containing 0.5% podofilox to external genitalia did not result in detectable serum levels. Applications of 0.1 to 1.5 mL resulted in peak serum levels of 1 to 17 ng/mL one to two hours after application. The elimination half-life ranged from 1.0 to 4.5 hours. The drug was not found to accumulate after multiple treatments^1.

CLINICAL STUDIES

In the first multicenter clinical study in 326 patients with anogenital warts, Condylox Gel 0.5% and its vehicle were applied in a double-blind fashion to comparable patient groups. Of the 260 patients with efficacy data, 176 were treated with Condylox Gel 0.5%. Patients applied Condylox Gel 0.5% twice daily for three consecutive days followed by a 4 day “rest” period.

At the end of 4 weeks, 38.4% of the patients had complete clearing of the wart tissue when treated with Condylox Gel 0.5%.

In the second multicenter clinical trial in 108 evaluable patients with anogenital warts, Condylox (podofilox) Topical Solution 0.5% was compared with Condylox Gel 0.5% for efficacy. As in the first clinical trial, patients applied Condylox Gel 0.5% twice daily for three consecutive days followed by a four day “rest” period.

Similar clearance rates were observed. At the end of 4 weeks, 25.6% of the patients had complete clearing of the wart tissue when treated with Condylox Gel 0.5%.

INDICATIONS AND USAGE

Condylox Gel 0.5% is indicated for the topical treatment of anogenital warts (external genital warts and perianal warts). This product is not indicated in the treatment of mucous membrane warts (see PRECAUTIONS).

Diagnosis

Although anogenital warts have a characteristic appearance, histopathologic confirmation should be obtained if there is any doubt of the diagnosis. Differentiating warts from squamous cell carcinoma and "Bowenoid papulosis" is of particular concern. Squamous cell carcinoma may also be associated with human papillomavirus which should not be treated with Condylox Gel 0.5%.

CONTRAINDICATIONS

Condylox Gel 0.5% is contraindicated for patients who develop hypersensitivity or intolerance to any components of the formulation.

WARNINGS

Correct diagnosis of the lesions to be treated is essential. See the Diagnosis subsection of the INDICATIONS AND USAGE section. Condylox Gel 0.5% is intended for cutaneous use only. Avoid contact with the eyes. If contact with the eyes occurs, patients should immediately flush the eyes with copious quantities of water and seek medical advice.

Drug Product is Flammable.

Keep Away from Open Flame.

PRECAUTIONS

General

Data are not available on the safe and effective use of this product for treatment of warts occurring on mucous membranes of the genital area (including the urethra, rectum and vagina). The recommended method of application, frequency of application, and duration of usage should not be exceeded (see DOSAGE AND ADMINISTRATION).

Information for Patients

Patients using Condylox Gel 0.5% should receive the following information and instructions. This information is intended to aid in the safe and effective use of this medication. It is not intended to disclose all possible adverse or intended effects.

1) This medication should be used only as directed by the health care provider. Patients should be instructed to wash their hands thoroughly before and after each application. It is for external use only. Avoid contact with the eyes.

2) Patients should be advised not to use this medication for any disorder other than for which it was prescribed.

3) Patients should report any signs of adverse reactions to the health care provider.

4) If no improvement is observed after 4 weeks of treatment, discontinue the medication and consult the health care provider.

Carcinogenesis, Mutagenesis and Impairment of Fertility

An 80-week carcinogenicity study in the mouse was performed using a 0.5% podofilox solution applied dermally at 0.04, 0.2 and 1.0 mg/kg/day. There were no differences between the podofilox treated mice at any dose level and vehicle control in the incidence of neoplasia. Published animal studies, in general, have not shown the drug substance, podofilox, to be carcinogenic.^2,3,4,5,6 There are published reports that, in mouse studies, crude podophyllin resin (containing podofilox) applied topically to the cervix produced changes resembling carcinoma in situ.^7 These changes were reversible at five weeks after cessation of treatment. In one reported experiment, epidermal carcinoma of the vagina and cervix was found in 1 out of 18 mice after 120 applications of podophyllin^8 (the drug was applied twice weekly over a 15-month period).

Podofilox was not mutagenic in the Ames plate reverse mutation assay at concentrations up to 5 mg/plate, with and without metabolic activation. No cell transformation related to potential oncogenicity was observed in BALB/3T3 cells after exposure to podofilox at concentrations up to 0.008 mcg/mL, without metabolic activation and 12 mcg/mL podofilox with metabolic activation. Results from the mouse micronucleus in vivo assay using podofilox 0.5% solution at doses up to 25 mg/kg (75 mg/m^2), indicate that podofilox should be considered a potential clastogen (a chemical that induces disruption and breakage of chromosomes).

Daily topical application of 0.5% podofilox solution at doses up to the equivalent of 0.2 mg/kg (1.18 mg/m^2, approximately equivalent to the human daily dose) to rats throughout gametogenesis, mating, gestation, parturition and lactation for two generations demonstrated no impairment of fertility.

Pregnancy

0.5% podofilox solution was not teratogenic in the rabbit following topical application of up to 0.21 mg/kg (2.85 mg/m^2, approximately 2 times the maximum human dose) once daily for 13 days. The scientific literature contains references that podofilox is embryotoxic in rats when administered intraperitoneally at a dose of 5 mg/kg (29.5 mg/m^2, approximately 19 times the recommended maximum human dose).^9 Teratogenicity and embryotoxicity have not been studied with intravaginal application. Many antimitotic drug products are known to be embryotoxic. There are no adequate and well-controlled studies in pregnant women. Condylox Gel 0.5% should be used during pregnancy only if the potential benefit justifies the potential risk to the fetus.

Nursing Mothers

It is not known whether this drug is excreted in human milk. Because of the potential for serious adverse reactions in nursing infants from podofilox, a decision should be made whether to discontinue nursing or to discontinue the drug, taking into account the importance of the drug to the mother.

Pediatric Use

Safety and effectiveness in pediatric patients have not been established.

ADVERSE REACTIONS

In clinical trials with Condylox Gel 0.5%, the following local adverse reactions were reported during the treatment of anogenital warts. The severity of local adverse reactions were predominantly mild or moderate and did not increase during the treatment period. Severe reactions were most frequent within the first 2 weeks of treatment.

Adverse Reaction | Mild | Moderate | Severe
Inflammation | 32.2% | 30.4% | 9.3%
Burning | 37.1% | 25.9% | 11.5%
Erosion | 27.0% | 20.8% | 8.9%
Pain | 23.7% | 20.4% | 11.5%
Itching | 32.2% | 16.0% | 7.8%
Bleeding | 19.2% | 3.0% | 0.7%

Other local adverse reactions reported included stinging (7%), and erythema (5%); less commonly reported local adverse events included desquamation, scabbing, discoloration, tenderness, dryness, crusting, fissures, soreness, ulceration, swelling/edema, tingling, rash, and blisters.

The most common systemic adverse event reported during the clinical studies was headache (7%).

OVERDOSAGE

Topically applied podofilox may be absorbed systemically (see CLINICAL PHARMACOLOGY section). Toxicity reported following systemic administration of podofilox in investigational use for cancer treatment included: nausea, vomiting, fever, diarrhea, bone marrow depression, and oral ulcers. Following 5 to 10 daily intravenous doses of 0.5 to 1 mg/kg/day, significant hematological toxicity occurred but was reversible.^10 Other toxicities occurred at lower doses. Toxicity reported following systemic administration of podophyllum resin included: nausea, vomiting, fever, diarrhea, peripheral neuropathy, altered mental status, lethargy, coma, tachypnea, respiratory failure, leukocytosis, pancytosis, hematuria, renal failure and seizures.^11 Treatment of topical overdosage should include washing the skin free of any remaining drug and symptomatic and supportive therapy.

DOSAGE AND ADMINISTRATION

The prescriber should ensure that the patient is fully aware of the correct method of therapy and identify which specific warts should be treated.

Apply twice daily for 3 consecutive days, then discontinue for 4 consecutive days. This one-week cycle of treatment may be repeated until there is no visible wart tissue or for a maximum of four cycles. If there is incomplete response after four treatment cycles, discontinue treatment and consider alternative treatment. Safety and effectiveness of more than four treatment cycles has not been established. There is no evidence to suggest that more frequent application will increase efficacy, but additional applications would be expected to increase the rate of local adverse reactions and systemic absorption.

Condylox Gel 0.5% should be applied to the warts with the applicator tip or finger. Application on the surrounding normal tissue should be minimized. Treatment should be limited to 10 cm^2 or less of wart tissue and to no more than 0.5 gram of the gel per day.

Care should be taken to allow the gel to dry before allowing the return of opposing skin surfaces to their normal positions. Patients should be instructed to wash their hands thoroughly before and after each application.

HOW SUPPLIED

Condylox Gel 0.5% is supplied as 3.5 grams of clear gel in aluminum tubes with an applicator tip. NDC 0023-6118-03. Store at 20-25°C (68-77°F). [See USP controlled room temperature.] Avoid excessive heat. Do not freeze.

Keep out of reach of children.

Rx only

REFERENCES

1. Von Krogh G. Podophyllotoxin in serum: Absorption subsequent to three day repeated applications of a 0.5% ethanolic preparation on condylomata acuminata. Sex Trans Disease 1982: 9: 26-33.
2. Berenblum I. The effect of podophyllotoxin on the skin of the mouse, with reference to carcinogenic, cocarcinogenic, and anticarcinogenic action. J Cancer Inst 11:839-841, 1951.
3. Kaminetzky HA, Swerdlow M. Podophyllin and the mouse cervix: assessment of carcinogenic potential. Am J Obst Gyn 95:486-490, 1965.
4. McGrew EA, Kaminetzky HA. The genesis of experimental cervical epithelial dysplasia. Am J Clin Path 35:538-545, 1961.
5. Roe FJC, Salaman MH. Further studies on incomplete carcinogenesis: triethylene melamine (T.E.M.) 1,2 benxanthracene and beta-propiolactone as initiators of skin tumor formation in the mouse. Brit J Cancer, 9:177-203, 1955.
6. Taper HS. Induction of the deficient acid DNAase activity in mouse interfollicular epidermis by croton oil as a possible tumor promoting mechanism. Zeitschrift fur Krebsforschung and Klinisch Onkologie (Cancer Research and Clinical Oncology, Berlin) 90:197-210, 1977.
7. Kaminetzky HA, McGrew EA, Phillips RL. Experimental cervical epithelial dysplasia. J Obst Gyn 14:1-10, 1959.
8. Kaminetzky HA, McGrew EA: Podophyllin and mouse cervix: Effect of long term application. Arch Path 73:481-485, 1962.
9. Thiersch JB. Effect of podophyllin (P) and podophylotoxine (PT.) on the rat litter in utero. Soc Exptl Biol Med Proc. 113:124-127, 1963.
10. Savel H.: Clinical experience with intravenous podophyllotoxin. Proc Amer Assoc Cancer Res, 1964; 5: 56.
11. Cassidy DE, Dewry J and Fanning JP: Podophyllum toxicity: A report of a fatal case and a review of the literature. J Toxicol Clinic Toxicol 1982: 19: 35-44.

For all medical inquiries contact:
AbbVie, Inc.
1-800-678-1605

Distributed by:
AbbVie, Inc.
North Chicago, IL 60064

Manufactured by:
DPT Laboratories, Ltd.
San Antonio, TX 78215

© 2024 AbbVie. All rights reserved.
CONDYLOX and its design are trademarks of Allergan Sales, LLC, an AbbVie company.

Content Updated: Jan2024

Patient Information

Condylox® Gel 0.5%

(podofilox gel)

Condylox Gel (podofilox gel) and Anogenital Warts

1. APPLY CONDYLOX GEL ONLY ON THE WARTS POINTED OUT BY YOUR DOCTOR.
2. YOU MAY FEEL SOME MILD TO MODERATE DISCOMFORT DURING TREATMENT.
3. STOP TREATMENT AND CALL YOUR DOCTOR IF YOU HAVE BLEEDING, SWELLING, OR EXCESSIVE PAIN, BURNING, OR ITCHING.
4. DO NOT USE MORE THAN TWO TIMES A DAY.
5. DO NOT USE FOR MORE THAN THREE DAYS IN A ROW.
6. DO NOT HAVE SEXUAL INTERCOURSE ON THE DAYS YOU ARE APPLYING CONDYLOX GEL.
7. WASH HANDS AFTER EVERY USE.

INTRODUCTION

Condylox Gel slowly kills external anogenital warts. The warts will change from a fleshy skin color to a dry, crusted, dead look, then disappear. Three out of four patients feel some burning or pain after they apply Condylox Gel. Other side effects may include redness, soreness, tenderness, and small sores. These usually go away within a week after Condylox Gel is stopped. If pain or other side effects bother you too much, stop applying Condylox Gel and contact your doctor.

HOW TO USE CONDYLOX GEL

Follow these and your doctor’s instructions carefully. Apply Condylox Gel only on the warts pointed out by your doctor. Do not use it on any other warts on or inside your body, or for any other skin growth.

1. Unscrew the entire applicator cap. Invert the cap and puncture the tube seal. Replace the applicator cap. To apply Condylox Gel, remove the protective cap on the applicator tip and apply to the warts using the applicator tip or finger. Make sure to replace the applicator cap tightly after use.

APPLY CONDYLOX GEL ONLY WHERE YOUR DOCTOR HAS INSTRUCTED YOU.

2. Apply a small amount of Condylox Gel to the wart(s). Do not get it on normal skin. If a wart is in a skin fold, spread the skin apart so you can reach the wart. A hand mirror can help sometimes. Let Condylox Gel dry before letting the skin folds return to their normal position. Wash your hands well with soap and water after you use Condylox Gel.

3. Apply Condylox Gel once in the morning and once in the evening for three days in a row. Then stop applying Condylox Gel and wait four days. Using Condylox Gel like this is called a treatment week. You should not wash Condylox Gel off the wart area unless you experience excessive pain, burning, or itching.

DO NOT APPLY CONDYLOX GEL MORE THAN TWICE EACH DAY OR FOR MORE THAN THREE DAYS IN A ROW. USING CONDYLOX GEL MORE OFTEN WILL NOT MAKE IT WORK BETTER BUT MAY INCREASE SIDE EFFECTS.

4. If the warts do not go away, repeat the Condylox Gel treatment for another week. You can use Condylox Gel up to four treatment weeks (REMEMBER: a treatment week is twice a day for three days, then four days with no treatment). Your doctor may ask you to come back for a check-up visit during treatment. If the warts have not gone away after four treatment weeks, stop applying Condylox Gel and contact your doctor.

IF THE AREA YOU ARE PUTTING CONDYLOX GEL ON IS BLEEDING OR SWOLLEN, OR IF THERE IS EXCESSIVE PAIN, BURNING OR ITCHING, STOP APPLYING CONDYLOX GEL AND CONTACT YOUR DOCTOR.

5. Anogenital warts can come back. If your warts come back, contact your doctor.

SPECIAL CAUTIONS

- Anogenital warts are contagious. You can give them to or get them from your sexual partner. Make sure your sexual partner has been checked for anogenital warts. Condoms may help prevent giving anogenital warts to your sexual partner. Do not have sexual intercourse for the three days you are applying Condylox Gel.
- Women should make sure to use birth control so they will not get pregnant while on Condylox Gel. The effects on the unborn baby are not known. Women can use Condylox Gel during their menstrual period.
- Condylox Gel is prescribed only for your external anogenital warts. Do not let anyone else use it.
- Drug Product is Flammable. Keep Away from Open Flame.

REMEMBER

- Always wash your hands after using Condylox Gel.
- Do not get it in your eyes. If you do, immediately flush your eyes with water and contact your doctor.
- Keep the tube cap tightly closed.
- Be sure to keep this and all medications out of the reach of children.

CONTACT YOUR DOCTOR IF YOU HAVE QUESTIONS ABOUT CONDYLOX® GEL.

Store at 20-25°C (68-77°F). [See USP controlled room temperature.]

Keep out of reach of children.

Rx only

For all medical inquiries contact:
AbbVie, Inc.
1-800-678-1605

Distributed by:
AbbVie, Inc.
North Chicago, IL 60064

Manufactured by:
DPT Laboratories, Ltd.
San Antonio, TX 78215

© 2024 AbbVie. All rights reserved.
CONDYLOX and its design are trademarks of Allergan Sales, LLC, an AbbVie company.

Content Updated: Jan2024

PRINCIPAL DISPLAY PANEL

NDC 0023-6118-03
3.5 g
Condylox® Gel 0.5%
(podofilox gel)
abbvie
FOR TOPICAL USE ONLY
Rx only